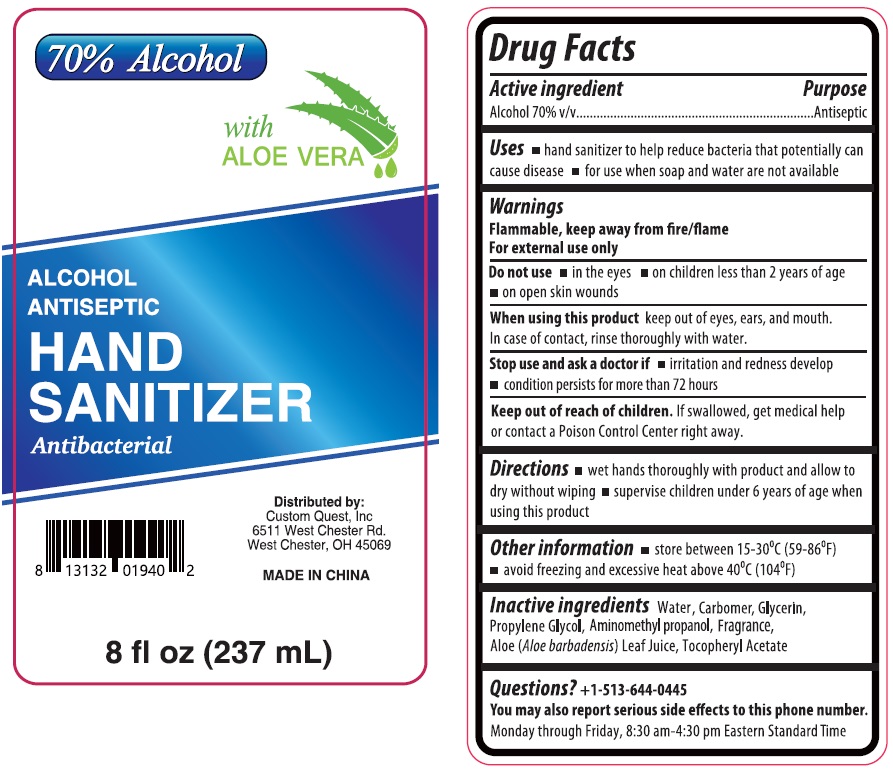 DRUG LABEL: ALCOHOL ANTISEPTIC HAND SANITIZER
NDC: 74876-656 | Form: GEL
Manufacturer: Custom Quest, Inc.
Category: otc | Type: HUMAN OTC DRUG LABEL
Date: 20231204

ACTIVE INGREDIENTS: ALCOHOL 70 mL/100 mL
INACTIVE INGREDIENTS: WATER; CARBOMER HOMOPOLYMER, UNSPECIFIED TYPE; GLYCERIN; PROPYLENE GLYCOL; AMINOMETHYLPROPANOL; ALOE VERA LEAF; .ALPHA.-TOCOPHEROL ACETATE

ALCOHOL ANTISEPTIC HAND SANITIZER

Active ingredient

Alcohol 70% v/v

Purpose

Antiseptic

Uses

• hand sanitizer to help reduce bacteria that potentially can cause disease • for use when soap and water are not available

Warnings

Flammable, keep away from fire/flame
For external use only

Do not use • in the eyes • on children less than 2 years of age • on open skin wounds

When using this product keep out of eyes, ears, and mouth. In case of contact, rinse thoroughly with water.

Stop use and ask a doctor if • irritation and redness develop • condition persists for more than 72 hours

Keep out of reach of children. If swallowed, get medical help or contact a Poison Control Center right away.

Directions

• wet hands thoroughly with product and allow to dry without wiping • supervise children under 6 years of age when using this product

Other information

• store between 15-30°C (59-86°F) • avoid freezing and excessive heat above 40°C (104°F)

Inactive ingredients

Water, Carbomer, Glycerin, Propylene Glycol, Aminomethyl propanol, Fragrance, Aloe (Aloe barbadensis) Leaf Juice, Tocopheryl Acetate

Questions?

+1-513-644-0445

You may also report serious side effects to this phone number.

Monday through Friday, 8:30 am-4:30 pm Eastern Standard Time

with ALOE VERA

Antibacterial

Distributed by:
Custom Quest, Inc
6511 West Chester Rd.
West Chester, OH 45069

MADE IN CHINA